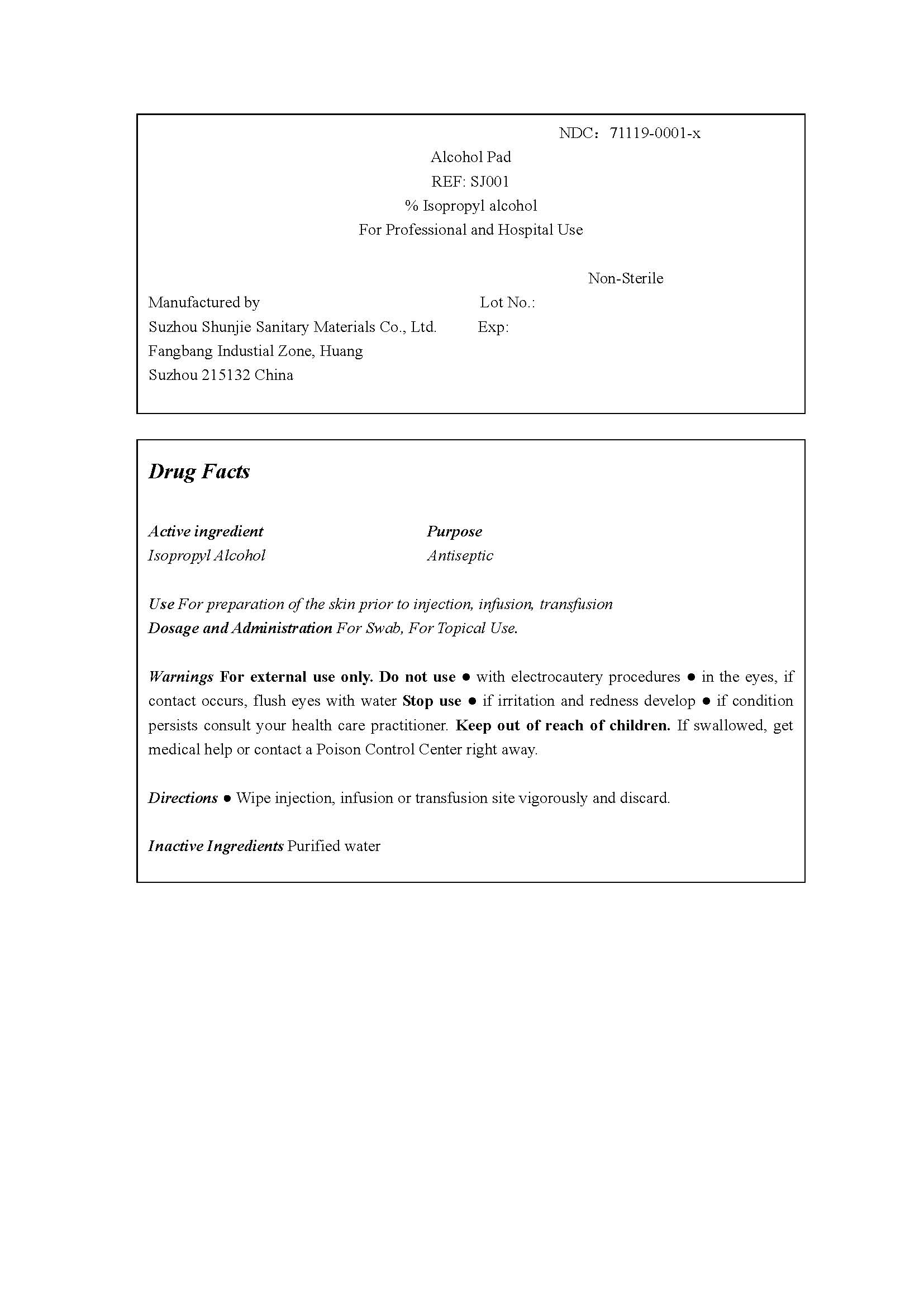 DRUG LABEL: Alcohol Pad
NDC: 71119-0001 | Form: SWAB
Manufacturer: Suzhou Shunjie Sanitary Materials Co., Ltd.
Category: otc | Type: HUMAN OTC DRUG LABEL
Date: 20160830

ACTIVE INGREDIENTS: ISOPROPYL ALCOHOL 0.7 1/1 1
INACTIVE INGREDIENTS: WATER 0.3 1/1 1

Alcohol Pad

Disclaimer: Most OTC drugs are not reviewed and approved by FDA, however they may be marketed if they comply with applicable regulations and policies. FDA has not evaluated whether this product complies.

Active Ingredient

70% Isopropyl Alcohol

Purpose

Antiseptic

USE

For preparation of the skin prior to injection, infusion, transfusion.

DOSAGE AND ADMINISTRATION

For Swab.

For Topical Use.

WARNING

For external use only.

DO NOT USE

● with electrocautery procedures.
● in the eyes, if contact occurs, flush eyes with water.

STOP USE

● if irritation and redness develop;

● if condition persists consult your health care practitioner.

KEEP OUT OF REACH OF CHIKDREN

If swallowed, get medical help or contact a Poison Control Center right away.

DIRECTIONS

● Wipe injection, infusion or transfusion site vigorously and discard.

INACTIVE INGREDIENT

Purified Water.